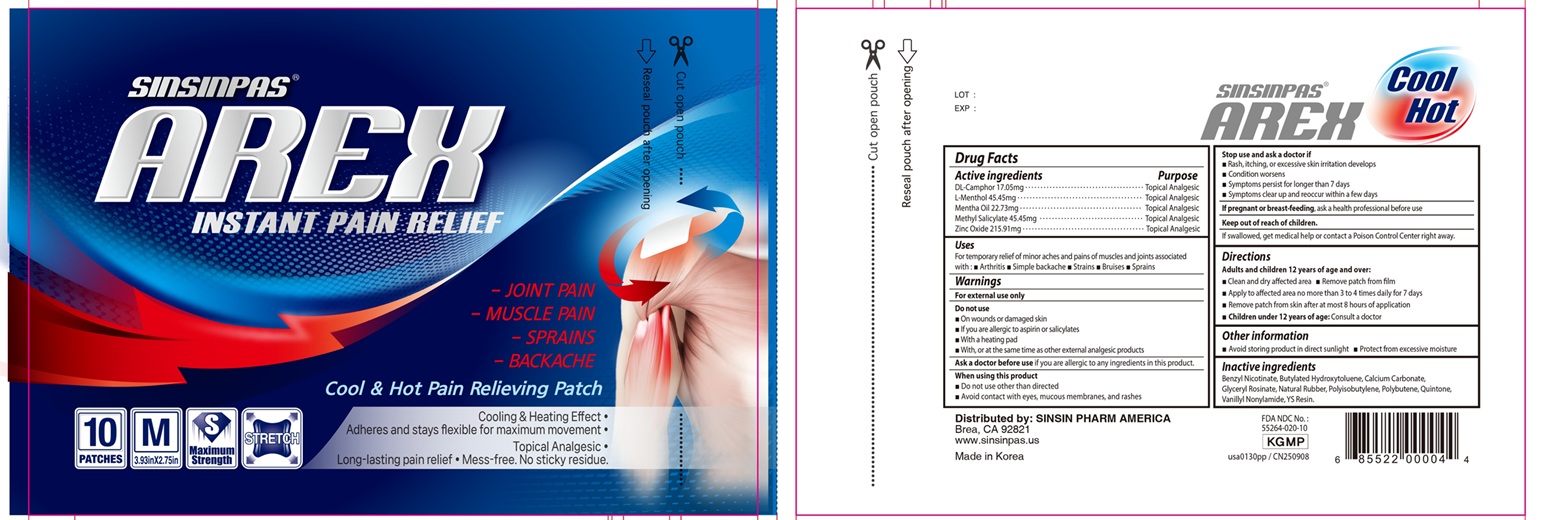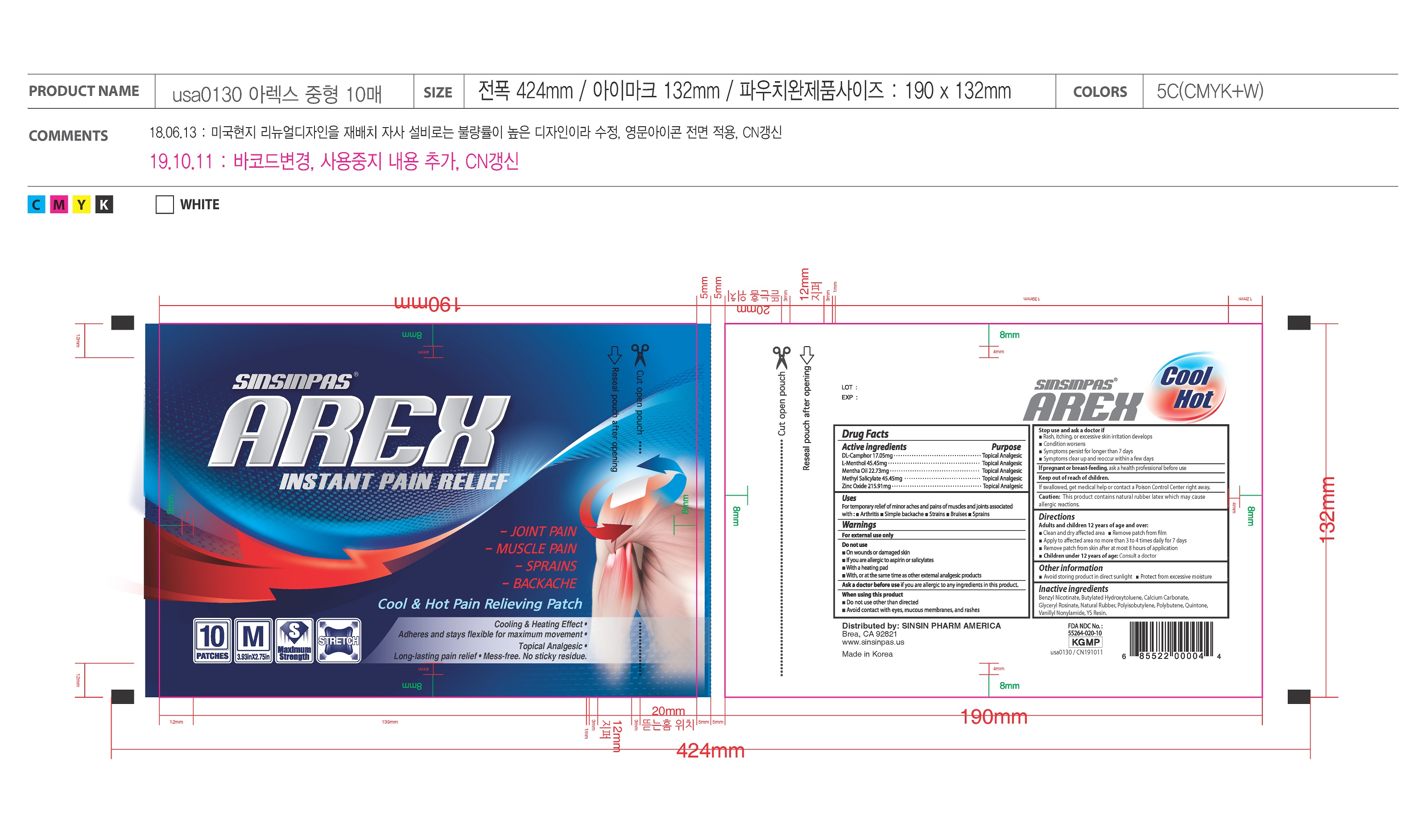 DRUG LABEL: AREX SINSIN PAS
NDC: 55264-020 | Form: PATCH
Manufacturer: Sinsin Pharmaceutical Co., Ltd.
Category: otc | Type: HUMAN OTC DRUG LABEL
Date: 20251007

ACTIVE INGREDIENTS: LEVOMENTHOL 45.45 mg/1 1; METHYL SALICYLATE 45.45 mg/1 1; ZINC OXIDE 215.91 mg/1 1; CAMPHOR (SYNTHETIC) 17.05 mg/1 1; PEPPERMINT OIL 22.73 mg/1 1
INACTIVE INGREDIENTS: BENZYL NICOTINAMIDE; BUTYLATED HYDROXYTOLUENE; CALCIUM CARBONATE; GLYCERIN; ROSIN; NATURAL LATEX RUBBER; POLYISOBUTYLENE (200000 MW); POLYBUTENE (1400 MW); NONIVAMIDE

Arex Sinsin Medium

Active ingredients

DL-Camphor 17.05mg

L-Menthol 45.45mg

Mentha Oil 22.73mg

Methyl Salicylate 45.45mg

Zinc Oxide 215.91mg

Purpose

Topical Analgesic

Uses

For temporary relief of minor aches and pains of muscles and joints associated with:

- arthritis
- simple backache
- strains
- bruises
- sprains

Do not use

- on wounds or damaged skin
- if you are allergic to aspirin or salicylates
- with a heating pad
- with, or at the same time as, other external analgesic products.

Ask a doctor before use

if you are allergic to any ingredients of this product

When using this product

- do not use otherwise than directed.
- avoid contact with the eyes, mucous membranes or rashes.

Stop use and ask a doctor if

- rash, itching or excessive skin irritation develops.
- conditions worsen.
- symptoms persist for more than 7 days.
- symptoms clear up and occur again within a few days.

Keep out of reach of children.

If swallowed, get medical help or contact a Poison Control Center right away.

Caution:

This product contains natural rubber latex which may cause allergic reactions.

Directions

Adults and children 12 years of age and over:

- Clean and dry affected area
- Remove patch from film.
- Apply to affected area not more than 3 to 4 times daily for 7 days.
- Remove patch from skin after at most 8 hours application.

Children under 12 years of age:

- Consult a doctor.

Other information

- avoid storing product in direct sunlight
- protect from excessive moisture

Inactive ingredients

Benzyl Nicothinamide, Butylated Hydroxytoluene, Calcium Carbonate, Glyceryl Rosinate, Natural Rubber, Polyisobutylene, Polybutene, Quintone, Vanillyl Nonylamide, YS Resin.

FDA NDC No.: 55264-020-10

Manufactured by:

SINSIN PHARM. CO., LTD.

90, Beomjigi-ro 141 beon-gil, Danwon-gu, Ansan-si, Gyeonggi-do, Korea

tel: 82-31-776-1140~3 http://www.sinsin.com